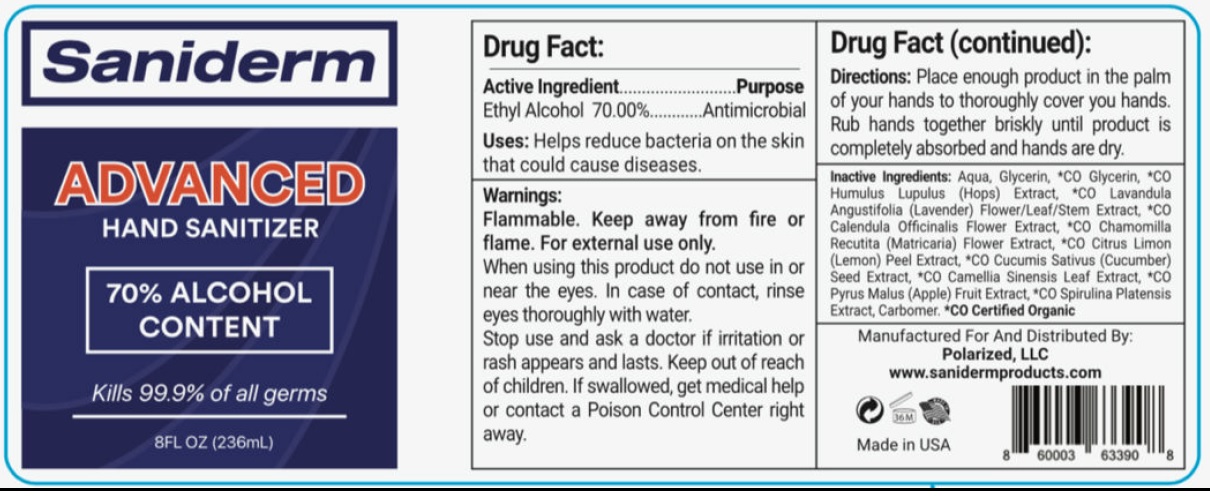 DRUG LABEL: Sanitizer Advanced Hand
NDC: 77449-001 | Form: GEL
Manufacturer: Glowbal Citizen LLC
Category: otc | Type: HUMAN OTC DRUG LABEL
Date: 20200514

ACTIVE INGREDIENTS: ALCOHOL 0.7 mL/1 mL
INACTIVE INGREDIENTS: WATER; GLYCERIN; HOPS; LAVANDULA ANGUSTIFOLIA SUBSP. ANGUSTIFOLIA FLOWERING TOP; CALENDULA OFFICINALIS FLOWER; CHAMOMILE; LEMON PEEL; CUCUMBER; GREEN TEA LEAF; APPLE; CARBOMER HOMOPOLYMER, UNSPECIFIED TYPE

Sanitizer Advanced Hand Gel

Active Ingredient

Ethyl Alcohol 70.00%

Purpose

Antimicrobial

Uses:

Helps reduce baceteria on the skin that colud cause diseases.

Warnings:

Flammable. Keep away from fire or flame. For external use only.

When using this product

do not use in or near the eyes. In case of contact, rinse eyes thoroughly with water.

Stop use and ask a doctor

if irritation or rash appears and lasts.

Keep out of reach of children.

If swallowed, get medical help or contact a Poison Control Center right away.

Directions:

Place enough product in the palm of your hands to thoroughly cover you hands. Rub hands together briskly until product is completely absorbed and hands are dry.

Inactive Ingredients:

Aqua, Glycerin, *CO Glycerin, *CO Humulus Lupulus (Hops) Extract, *Co Lavandula Angustifolia (Lavender) Flower/Leaf/Stem Extract, *CO Calendula Officinalis Flower Extract, *CO Chamomilla Recutita (Matricaria) Flower Extract, *CO Citrus Limon (Lemon) Peel Extract, *CO Camellia Sativus (Cucumber) Seed Extract, *CO Camellia Sinensis Leaf Extract, *CO Pyrus Malus (Apple) Fruit Extract, *CO Spirulina Platensis Extract, Carbomer. *CO Certified Organic